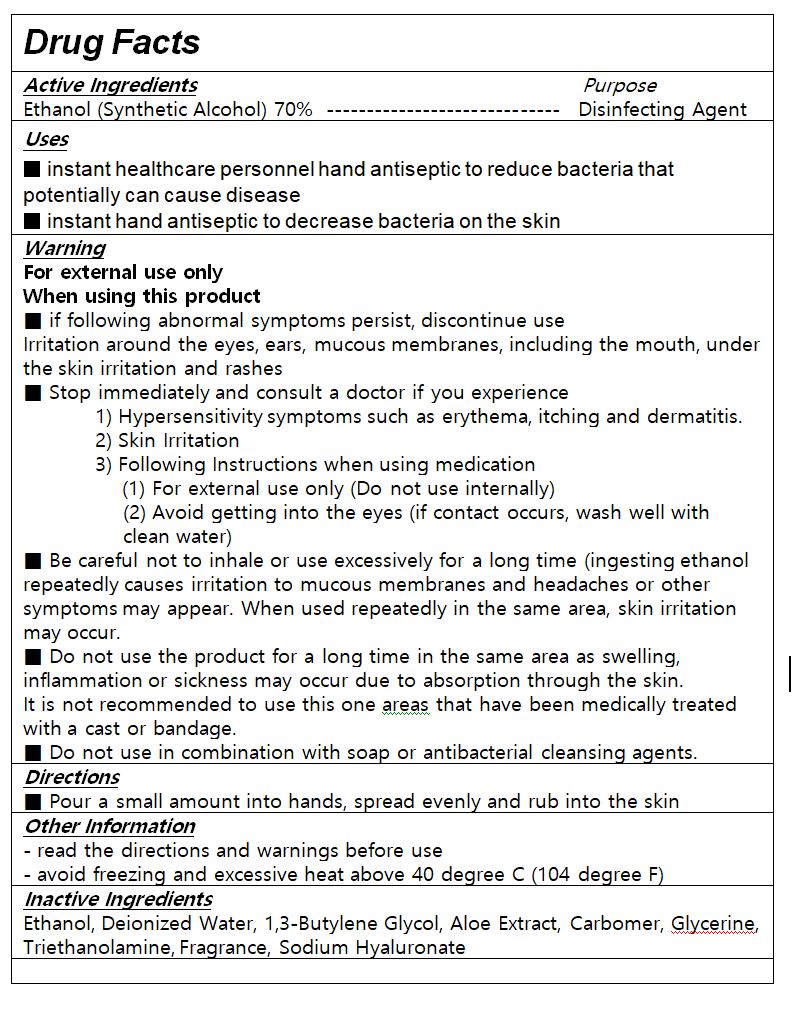 DRUG LABEL: Drs Clean Hand gel
NDC: 75193-0001 | Form: GEL
Manufacturer: EROOM FACTORY Co., Ltd.
Category: otc | Type: HUMAN OTC DRUG LABEL
Date: 20200412

ACTIVE INGREDIENTS: ALCOHOL 70 mL/100 mL
INACTIVE INGREDIENTS: ALOE VERA LEAF; HYALURONATE SODIUM; CARBOMER 940; WATER

Drug Facts

ACTIVE INGREDIENT

alcohol

INACTIVE INGREDIENT

Ethanol, Deionized Water, 1,3-Butylene Glycol, Aloe Extract, Carbomer, Glycerine, Triethanolamine, Fragrance, Sodium Hyaluronate

PURPOSE

Antimicrobial

KEEP OUT OF REACH OF THE CHILDREN

WARNINGS

■ Flammable. Keep away from fire or flame.

■ For external use only.

■ Do not use in eyes.

■ lf swallowed, get medical help promptly.

■ Stop use, ask doctor lf irritation occurs.

■ Keep out of reach of children.

DOSAGE AND ADMINISTRATION

for external use only